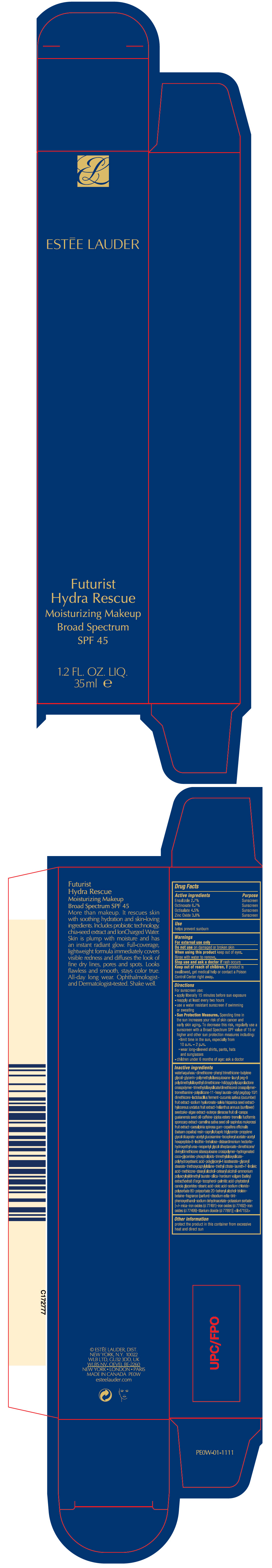 DRUG LABEL: FUTURIST HYDRA RESCUE MOISTURIZING MAKEUP BROAD SPECTRUM SPF 45
NDC: 11559-058 | Form: LIQUID
Manufacturer: ESTEE LAUDER INC
Category: otc | Type: HUMAN OTC DRUG LABEL
Date: 20240813

ACTIVE INGREDIENTS: ENSULIZOLE 27 mg/1 mL; OCTINOXATE 67 mg/1 mL; OCTISALATE 45 mg/1 mL; ZINC OXIDE 38 mg/1 mL
INACTIVE INGREDIENTS: HYALURONATE SODIUM; CHIA SEED; SELENICEREUS UNDATUS FRUIT; HELIANTHUS ANNUUS SEEDCAKE; ACAI OIL; CARAPA GUIANENSIS SEED OIL; CAFFEINE; TREMELLA FUCIFORMIS FRUITING BODY; CAMELINA SATIVA SEED OIL; SAPINDUS MUKOROSSI FRUIT; CAESALPINIA SPINOSA RESIN; COPAIFERA OFFICINALIS RESIN; MEDIUM-CHAIN TRIGLYCERIDES; PROPYLENE GLYCOL DICAPRATE; N-ACETYLGLUCOSAMINE; .ALPHA.-TOCOPHEROL ACETATE; ACETYL HEXAPEPTIDE-8; TREHALOSE; DISTEARDIMONIUM HECTORITE; HYDROXYETHYL UREA; NEOPENTYL GLYCOL DIHEPTANOATE; HYDROGENATED COCO-GLYCERIDES; LECITHIN, SOYBEAN; POLYGLYCERYL-4 ISOSTEARATE; GLYCERYL MONOSTEARATE; TRIETHOXYCAPRYLYLSILANE; TRIETHYL CITRATE; LAURETH-7; LINOLEIC ACID; METHICONE (20 CST); STEARYL ALCOHOL; CETOSTEARYL ALCOHOL; SODIUM CHLORIDE; POLYSORBATE 80; POLYSORBATE 20; DOCOSANOL; GLYCERYL TRIOLEATE; BETAINE; EDETATE DISODIUM ANHYDROUS; BUTYLATED HYDROXYTOLUENE; PHENOXYETHANOL; SODIUM DEHYDROACETATE; POTASSIUM SORBATE; MICA; FERRIC OXIDE RED; FERRIC OXIDE YELLOW; FERROSOFERRIC OXIDE; TITANIUM DIOXIDE; AMMONIUM POLYACRYLOYLDIMETHYL TAURATE (55000 MPA.S); SILICON DIOXIDE; BARLEY; TOCOPHEROL; PALMITIC ACID; STEARIC ACID; OLEIC ACID; WATER; DIMETHICONE; PHENYL TRIMETHICONE; BUTYLENE GLYCOL; GLYCERIN; POLYMETHYLSILSESQUIOXANE (4.5 MICRONS); LAURYL PEG-9 POLYDIMETHYLSILOXYETHYL DIMETHICONE; TROMETHAMINE; DIMETHICONE/VINYL DIMETHICONE CROSSPOLYMER (SOFT PARTICLE); HEXYL LAURATE; LIMOSILACTOBACILLUS REUTERI; CUCUMBER

FUTURIST HYDRA RESCUE MOISTURIZING MAKEUP BROAD SPECTRUM SPF 45

Drug Facts

ACTIVE INGREDIENT

Active ingredients | Purpose
Ensulizole 2.7% | Sunscreen
Octinoxate 6.7% | Sunscreen
Octisalate 4.5% | Sunscreen
Zinc Oxide 3.8% | Sunscreen

Use

helps prevent sunburn

Warnings

For external use only

Do not use on damaged or broken skin

When using this product keep out of eyes.

Rinse with water to remove.

Stop use and ask a doctor if rash occurs

Keep out of reach of children. If product is swallowed, get medical help or contact a Poison Control Center right away.

Directions

For sunscreen use:

- apply liberally 15 minutes before sun exposure
- reapply at least every two hours
- use a water resistant sunscreen if swimming or sweating
- Sun Protection Measures. Spending time in the sun increases your risk of skin cancer and early skin aging. To decrease this risk, regularly use a sunscreen with a Broad Spectrum SPF value of 15 or higher and other sun protection measures including:
  - limit time in the sun, especially from 10 a.m. – 2 p.m.
  - wear long-sleeved shirts, pants, hats and sunglasses
- children under 6 months of age: ask a doctor

Inactive ingredients

water\aqua\eau • dimethicone • phenyl trimethicone • butylene glycol • glycerin • polymethylsilsesquioxane • lauryl peg-9 polydimethylsiloxyethyl dimethicone • hdi/ppg/polycaprolactone crosspolymer • trimethylsiloxysilicate/dimethiconol crosspolymer • tromethamine • polysilicone-11 • hexyl laurate • cetyl peg/ppg-10/1 dimethicone • lactobacillus ferment • cucumis sativus (cucumber) fruit extract • sodium hyaluronate • salvia hispanica seed extract • hylocereus undatus fruit extract • helianthus annuus (sunflower) seedcake • algae extract • euterpe oleracea fruit oil • carapa guaianensis seed oil • caffeine • jojoba esters • tremella fuciformis sporocarp extract • camelina sativa seed oil • sapindus mukorossi fruit extract • caesalpinia spinosa gum • copaifera officinalis (balsam copaiba) resin • caprylic/capric triglyceride • propylene glycol dicaprate • acetyl glucosamine • tocopheryl acetate • acetyl hexapeptide-8 • lecithin • trehalose • disteardimonium hectorite • hydroxyethyl urea • neopentyl glycol diheptanoate • dimethicone/divinyldimethicone silsesquioxane crosspolymer • hydrogenated coco-glycerides • phospholipids • trimethylsiloxysilicate • polyhydroxystearic acid • polyglyceryl-4 isostearate • glyceryl stearate • triethoxycaprylylsilane • triethyl citrate • laureth-7 • linoleic acid • methicone • stearyl alcohol • cetearyl alcohol • ammonium polyacryloyldimethyl taurate • silica • hordeum vulgare (barley) extract\extrait d'orge • tocopherol • palmitic acid • phytosteryl canola glycerides • stearic acid • oleic acid • sodium chloride • polysorbate 80 • polysorbate 20 • behenyl alcohol • triolein • betaine • fragrance (parfum) • disodium edta • bht • phenoxyethanol • sodium dehydroacetate • potassium sorbate • [+/- mica • iron oxides (ci 77491) • iron oxides (ci 77492) • iron oxides (ci 77499) • titanium dioxide (ci 77891)] <iln47153>

Other information

protect the product in this container from excessive heat and direct sun

PRINCIPAL DISPLAY PANEL - 35 ml Tube Carton

ESTĒE LAUDER

Futurist
Hydra Rescue
Moisturizing Makeup
Broad Spectrum
SPF 45

1.2 FL. OZ. LIQ.
35ml ｅ